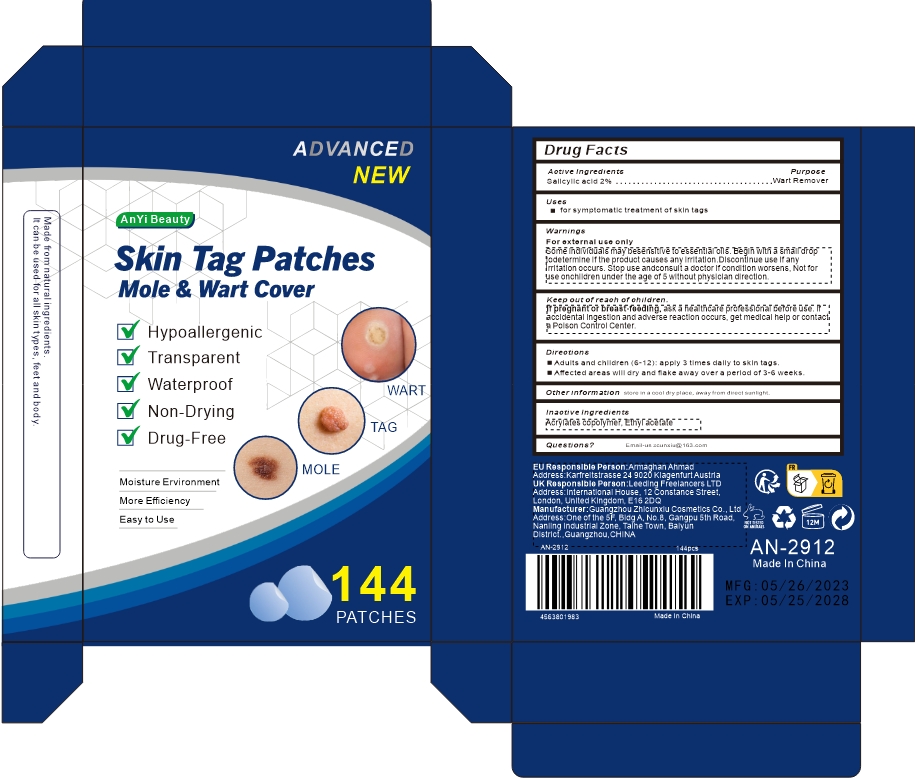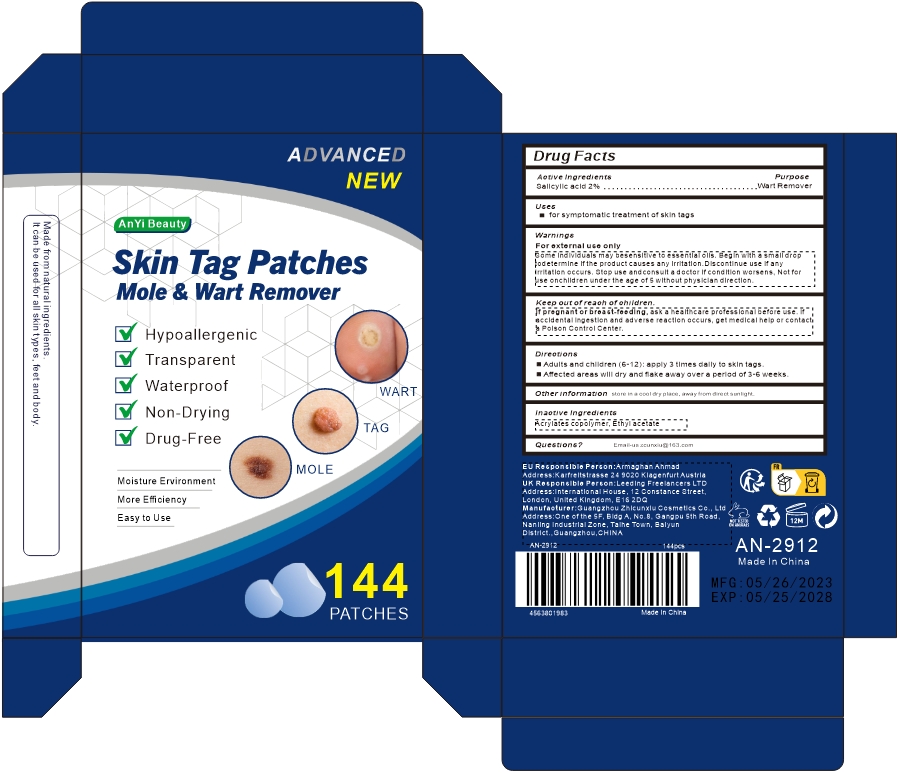 DRUG LABEL: AnYi Beauty Skin Tag Patches Mole  Wart Remover
NDC: 84037-0016 | Form: PATCH
Manufacturer: Guangzhou Zhicunxiu Cosmetics Co., Ltd
Category: otc | Type: HUMAN OTC DRUG LABEL
Date: 20240429

ACTIVE INGREDIENTS: SALICYLIC ACID 20 mg/1 1
INACTIVE INGREDIENTS: ETHYL ACETATE

AnYi Beauty Skin Tag Patches Mole & Wart Remover

Active Ingredient

Salicylic acid 2%

Purpose

wart remover

Uses

for symptomatic treatment of skin tags

Warnings

For external use only

Some individuals may besensitive to essential oils. Begin with a small drop todetermine if the product causes any irritation.Discontinue use if any irritation occurs. Stop use andconsult a doctor if condition worsens, Not for use onchildren under the age of 5 without physician direction.

Keep out of reach of children.

lf pregnant or breast-feeding,ask a healthcare professional before use. lf accidental ingestion and adverse reaction occurs, get medical help or contact a Poison Control Center.

Directions

- Adults and children (6-12): apply 3 times daily to skin tags.
- Affected areas will dry and flake away over a period of 3-6 weeks.

Other Information

store in a cool dry place, away from direct sunlight.

Inactive ingredients

Acrylates copolymer, Ethyl acetate

Questions?

Email-us zcunxiu@163.com